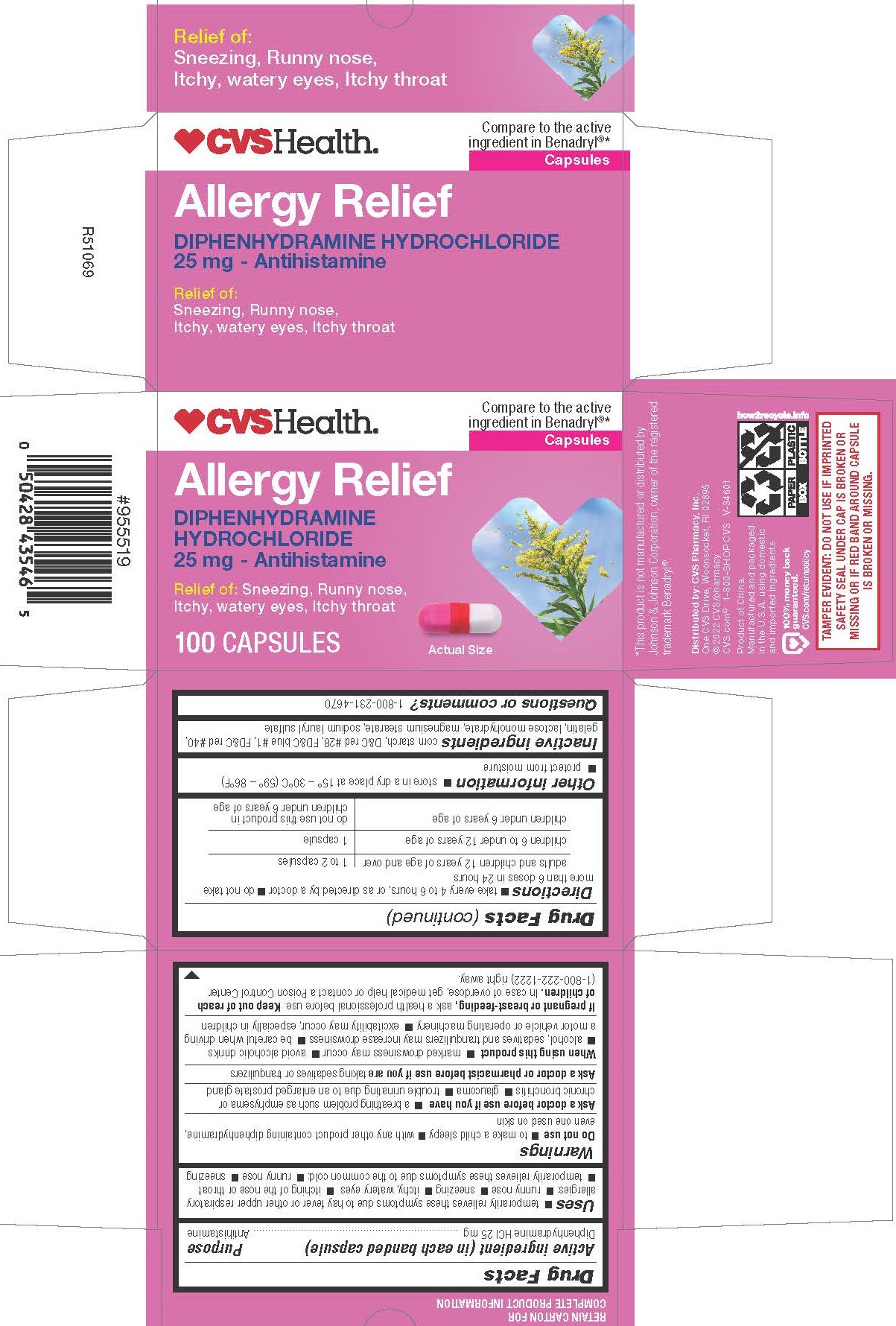 DRUG LABEL: Diphenhydramine Hydrochloride
NDC: 51316-835 | Form: CAPSULE
Manufacturer: CVS Pharmacy, Inc
Category: otc | Type: HUMAN OTC DRUG LABEL
Date: 20241202

ACTIVE INGREDIENTS: DIPHENHYDRAMINE HYDROCHLORIDE 25 mg/1 1
INACTIVE INGREDIENTS: MAGNESIUM STEARATE; STARCH, CORN; D&C RED NO. 28; GELATIN; LACTOSE MONOHYDRATE; SODIUM LAURYL SULFATE; FD&C BLUE NO. 1; FD&C RED NO. 40

0835K-CVS

Drug Facts

Active ingredient (in each banded capsule)

Diphenhydramine HCI 25 mg

Purpose

Antihistamine

Uses

 temporarily relieves these symptoms due to hay fever or other upper respiratory allergies:  runny nose  sneezing  itchy, watery eyes  itching of the nose or throat
 temporarily relieves these symptoms due to the common cold:  runny nose  sneezing

WARNINGS

Do not use

 to make a child sleepy

 with any other product containing diphenhydramine, even one used on skin

Ask a doctor before use if you have

 a breathing problem such as emphysema or chronic bronchitis

 glaucoma

 trouble urinating due to an enlarged prostate gland

Ask a doctor or pharmacist before use if you are taking sedatives or tranquilizers

When using this product

 marked drowsiness may occur

 avoid alcoholic drinks
 alcohol, sedatives and tranquilizers may increase drowsiness

 be careful when driving a motor vehicle or operating machinery

 excitability may occur, especially in children

PREGNANCY OR BREAST FEEDING

If pregnant or breast-feeding, ask a health professional before use.

Keep out of reach of children.

OVERDOSAGE

In case of overdose, get medical help or contact a Poison Control Center (1-800-222-1222) right away.

DIrections

 take every 4 to 6 hours, or as directed by a doctor

 do not take more than 6 doses in 24 hours

adults and children 12 years of age and over | 1 to 2 capsules
children 6 to under 12 years of age | 1 capsule
children under 6 years of age | do not use this product in children under 6 years of age

Other information

 store in a dry place at 15° – 30°C (59° – 86°F)
 protect from moisture

INACTIVE INGREDIENT

corn starch, D&C red #28, FD&C blue #1, FD&C red #40, gelatin, lactose monohydrate, magnesium stearate, sodium lauryl sulfate

Questions or comments? 1-800-231-4670

*This product is not manufactured or distributed by Johnson & Johnson Corporation, owner of the registered trademark Benadryl®.

Distributed by: CVS Pharmacy, Inc.
One CVS Drive, Woonsocket, RI 02895
© 2022 CVS/pharmacy
CVS.com® 1-800-SHOP CVS V-34601

Product of China. Manufactured and packaged in the U.S.A. using domestic and imported ingredients.

TAMPER EVIDENT: DO NOT USE IF IMPRINTED SAFETY SEAL UNDER CAP IS BROKEN OR MISSING OR IF RED BAND AROUND CAPSULE IS BROKEN OR MISSING

PACKAGE LABEL

Compare to the active ingredient in Benadryl®*

Allergy Relief

DIPHENHYDRAMINE HYDROCHLORIDE
25 mg - Antihistamine

Relief of: Sneezing, Runny nose, Itchy, watery eyes, Itchy throat

100 CAPSULES